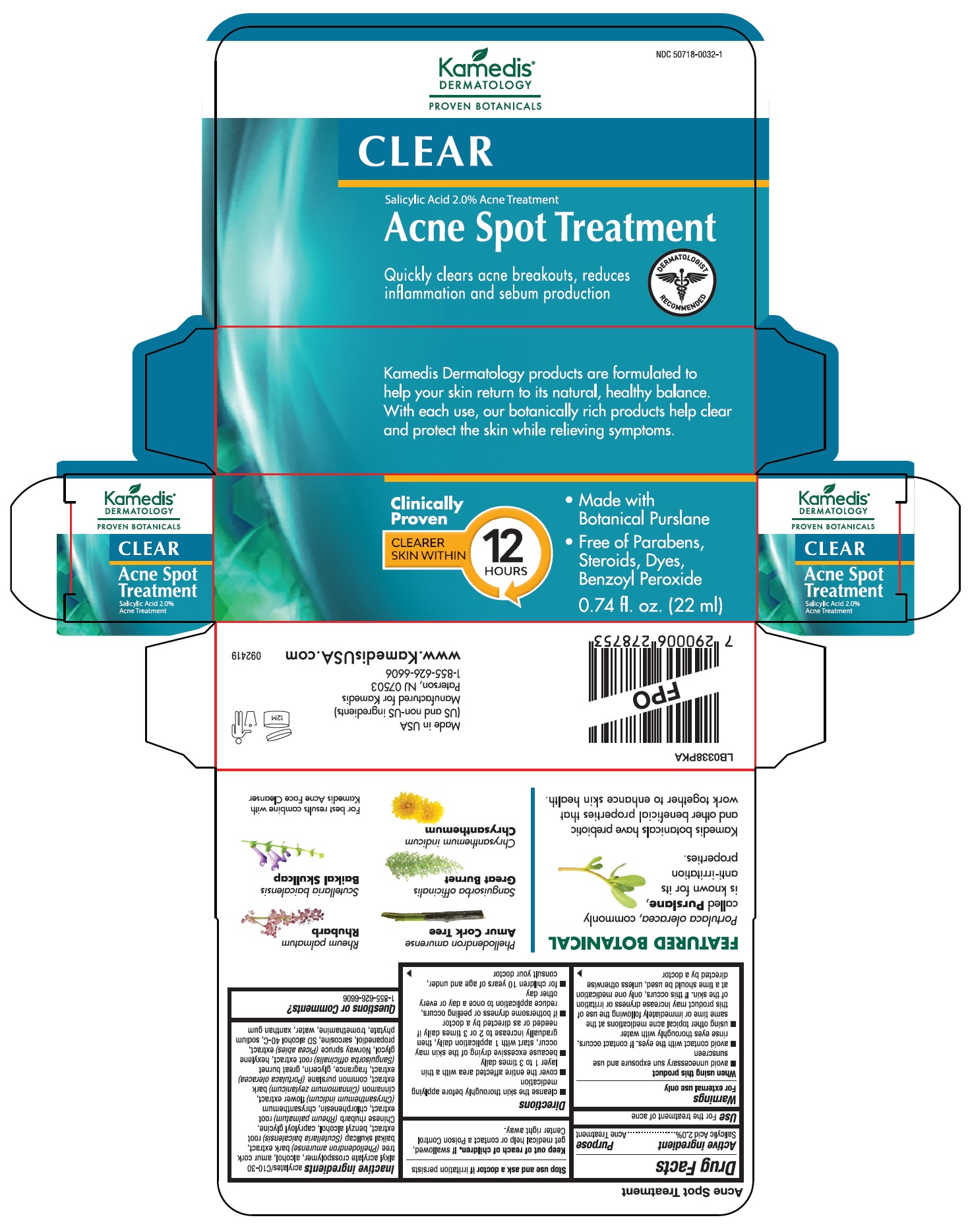 DRUG LABEL: Clear Acne Spot Treatment
NDC: 50718-0032 | Form: LIQUID
Manufacturer: Kamedis
Category: otc | Type: HUMAN OTC DRUG LABEL
Date: 20240207

ACTIVE INGREDIENTS: SALICYLIC ACID 28.8 mg/1 mL
INACTIVE INGREDIENTS: (C10-C30)ALKYL METHACRYLATE ESTER; ALCOHOL; PHELLODENDRON AMURENSE BARK; SCUTELLARIA BAICALENSIS ROOT; BENZYL ALCOHOL; CAPRYLOYL GLYCINE; CHLORPHENESIN; CHRYSANTHEMUM INDICUM FLOWER; PURSLANE; GLYCERIN; RHEUM PALMATUM ROOT; SANGUISORBA OFFICINALIS ROOT; HEXYLENE GLYCOL; PICEA ABIES WOOD; PROPANEDIOL; SARCOSINE; HEXASODIUM PHYTATE; TROMETHAMINE; WATER; XANTHAN GUM; CINNAMON BARK OIL

Clear Acne Spot Treatment

Drug Facts

Active Ingredient

Salicylic Acid 2.0%

Purpose

Acne Treatment

Use

- For the treatment of acne

Warnings

For external use only

When using this product

- avoid unnecessary sun exposure and use sunscreen
- avoid contact with the eyes. If contact occurs, rinse eyes thoroughly with water
- using other topical acne medication at the same time or immediately following the use of this product may increase dryness or irritation of the skin. If this occurs, only one medication at a time should be used, unless otherwise directed by a doctor

Stop use and ask a doctor

- if irritation persists

Keep out of reach of children

- If swallowed, get medical help or contact a Poison Control Center right away.

Directions

- cleanse the skin thoroughly before applying medication
- cover the entire affected area with a thin layer 1 to 3 times daily
- because excessive drying of the skin may occur, start with 1 application daily, then gradually increase to 2 or 3 times daily if needed or as directed by a doctor
- if bothersome dryness or peeling occurs, reduce application to once a day or every other day
- for children under 10 years of age and under, consult your physician

Inactive Ingredients

acrylates/C10-30 alkyl acrylate crosspolymer, alcohol, amur cork tree (Phellodendron amurense) bark extract, baikal skullcap (Scutellaria baicalensis) root extract, benzyl alcohol, capryloyl glycine, Chinese rhubarb (Rheum palmatum) root extract, chlorphenesin, chrysanthemum (Chrysanthemum indicum) flower extract, cinnamon (Cinnamomum zeylanicum) bark extract, common purslane (Portulaca oleracea) extract, fragrance, glycerin, great burnet (Sanguisorba officinalis) root extract, hexylene glycol, Norway spruce (Picea abis) extract, propanediol, sarcosine, SD Alcohol 40-C, sodium phytate, tromethamine, water, xanthan gum

Questions or Comments?

1-855-626-6606

Made in USA
(US and non-US ingredients)
Manufactured for Kamedis
Paterson, NJ 07503
1-855-626-6606

www.kamedisUSA.com